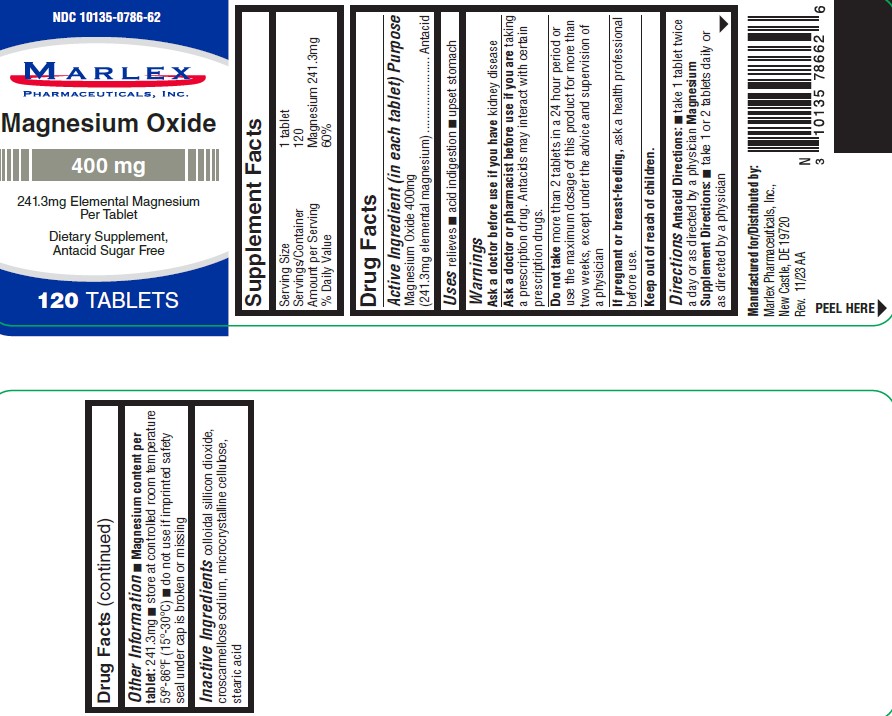 DRUG LABEL: Magnesium Oxide
NDC: 10135-786 | Form: TABLET
Manufacturer: Marlex Pharmaceuticals Inc
Category: otc | Type: HUMAN OTC DRUG LABEL
Date: 20251114

ACTIVE INGREDIENTS: MAGNESIUM OXIDE 400 mg/1 1
INACTIVE INGREDIENTS: STEARIC ACID; SILICON DIOXIDE; CROSCARMELLOSE SODIUM; MICROCRYSTALLINE CELLULOSE

Magnesium Oxide

MAGNESIUM OXIDE 400MG- magnesium oxide 400mg tablet

Marlex Pharmaceuticals, Inc.

Disclaimer: Most OTC drugs are not reviewed and approved by FDA, however they may be marketed if they comply with applicable regulations and policies. FDA has not evaluated whether this product complies.

----------

Magnesium Oxide Tablets

ACTIVE INGREDIENT (In each tablet)

Magnesium Oxide 400mg (241.3mg elemental magnesium)

Purpose

Antacid

USES

- relieves
- acid indigestion
- upset stomach

WARNINGS

Ask a doctor if you have

kidney disease

Ask a doctor or pharmacist before use if you are

taking a prescription drug. Antacids may interact with certain prescription drugs.

Do not take

more than 2 tablets in a 24 hour period or use the maximum dosage of this product for more than two weeks, except under the advise and supervision of a physician

If pregnant or breast-feeding,

ask a health professional before use.

DIRECTIONS

Antacid Directions:

- take 1 tablet twice a day or as directed by a physician

Magnesium Supplement Directions:

- take 1 to 2 tablets daily or as directed by a physician

OTHER INFORMATION

- Magnesium content per tablet:241.3mg
- store at room temperature 59°-86° F (15°-30°C)
- do not use if imprinted safety seal under cap is broken or missing

INACTIVE INGREDIENTS

colloidal silicon dioxide, croscarmellose sodium, microcrystalline cellulose, stearic acid

Manufactured for/ Distributed by:
Marlex Pharmaceuticals, Inc.
New Castle, DE 19720

Rev. 11/23 AA

PRINCIPAL DISPLAY PANEL

NDC 10135-0786-62
Magnesium Oxide
400 mg
120 TABLETS